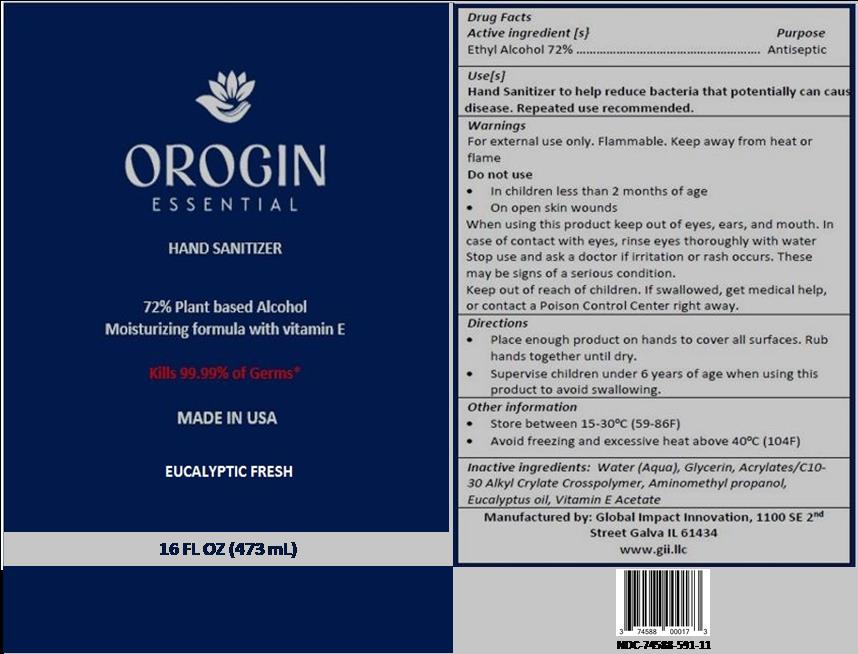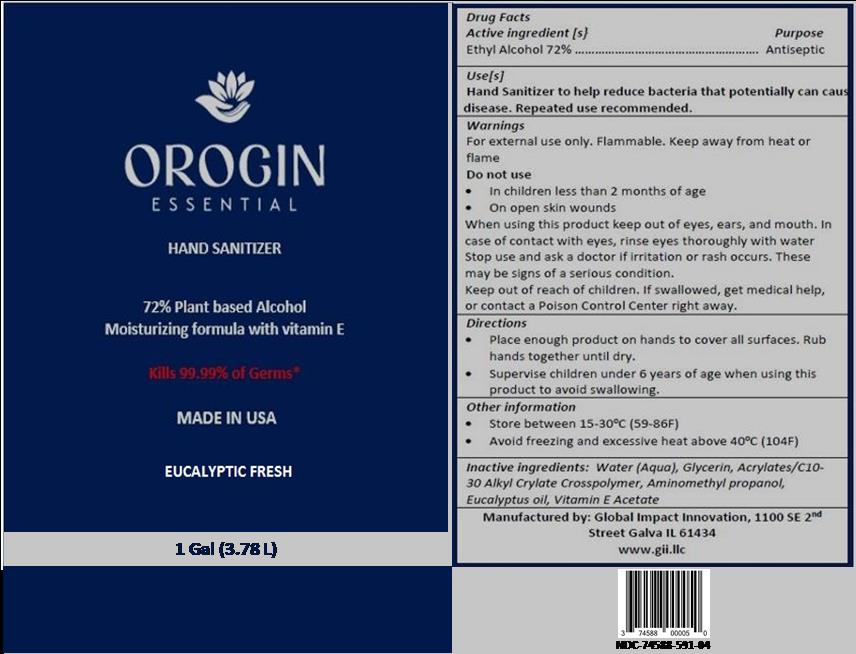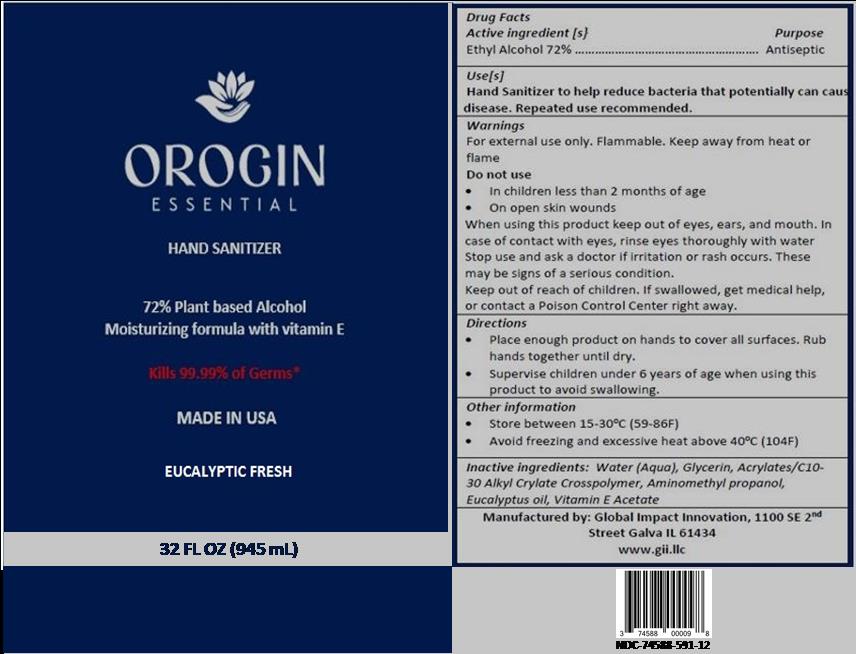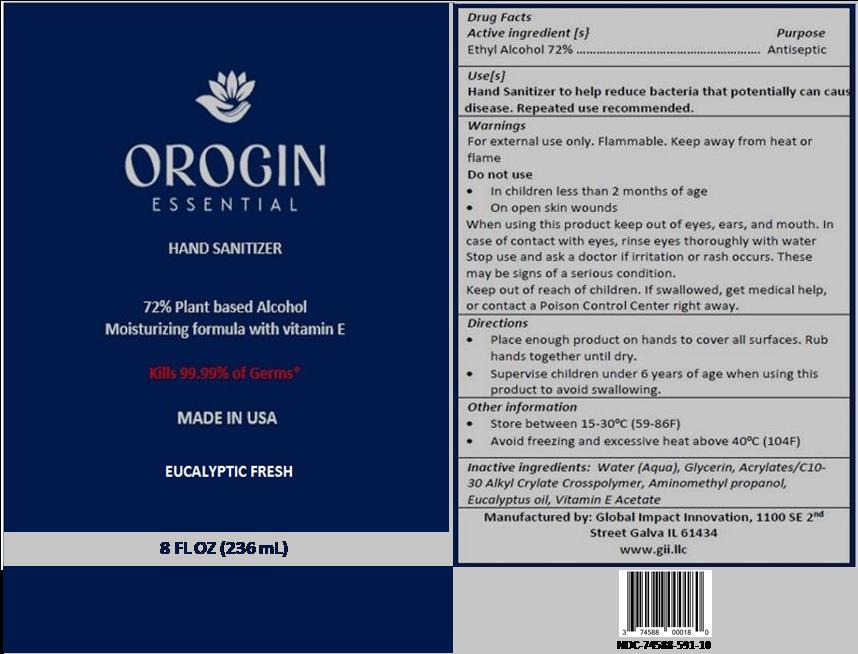 DRUG LABEL: Orogin Essential Eucalyptic Fresh
NDC: 74588-591 | Form: SOLUTION
Manufacturer: Global Impact Innovation LLC
Category: otc | Type: HUMAN OTC DRUG LABEL
Date: 20200601

ACTIVE INGREDIENTS: ALCOHOL 170.3436 mL/236.588 mL
INACTIVE INGREDIENTS: GLYCERIN 3.4305 mL/236.588 mL; .ALPHA.-TOCOPHEROL ACETATE 0.1183 mL/236.588 mL; WATER 55.2945 mL/236.588 mL; EUCALYPTOL 0.349 mL/236.588 mL; AMINOMETHYLPROPANOL 0.3312 mL/236.588 mL; CARBOMER 940 6.7213 mL/236.588 mL

Active Ingredient(s)

Alcohol 80% v/v. Purpose: Antiseptic

Purpose

Antiseptic, Hand Sanitizer

Use

Hand Sanitizer to help reduce bacteria that potentially can cause disease. For use when soap and water are not available.

Warnings

For external use only. Flammable. Keep away from heat or flame

Do not use

- in children less than 2 months of age
- on open skin wounds

When using this product keep out of eyes, ears, and mouth. In case of contact with eyes, rinse eyes thoroughly with water.
Stop use and ask a doctor if irritation or rash occurs. These may be signs of a serious condition.
Keep out of reach of children. If swallowed, get medical help or contact a Poison Control Center right away.

Stop use and ask a doctor if irritation or rash occurs. These may be signs of a serious condition.

Keep out of reach of children. If swallowed, get medical help or contact a Poison Control Center right away.

Directions

- Place enough product on hands to cover all surfaces. Rub hands together until dry.
- Supervise children under 6 years of age when using this product to avoid swallowing.

Other information

- Store between 15-30C (59-86F)
- Avoid freezing and excessive heat above 40C (104F)

Inactive ingredients

Water, Glycerin, Acrylates/C10-30 Alkyl Cryalate Crosspolymer, Aminomethylpropanol, Vitamin E Acetate, Eucalyptus Oil

Package Label - Principal Display Panel

236 mL NDC: 74588-591-10

473 mL NDC: 74588-591-11

945 mL NDC: 74588-591-12

3.78 L NDC: 74588-591-04